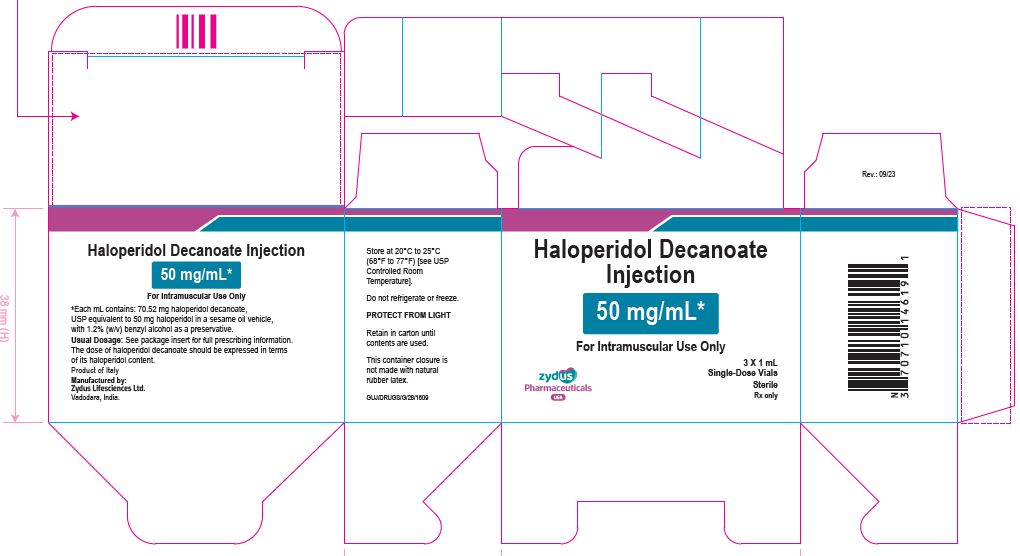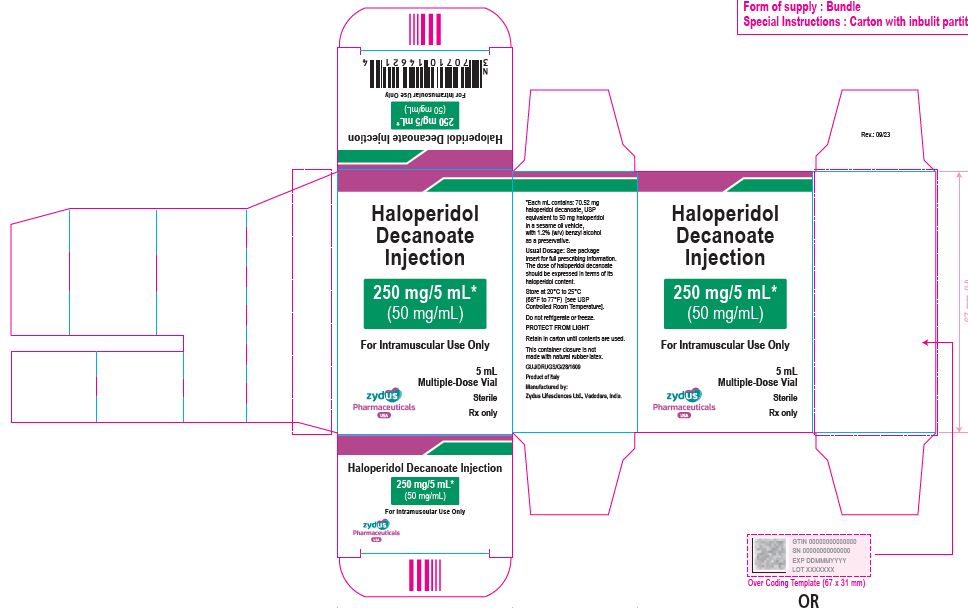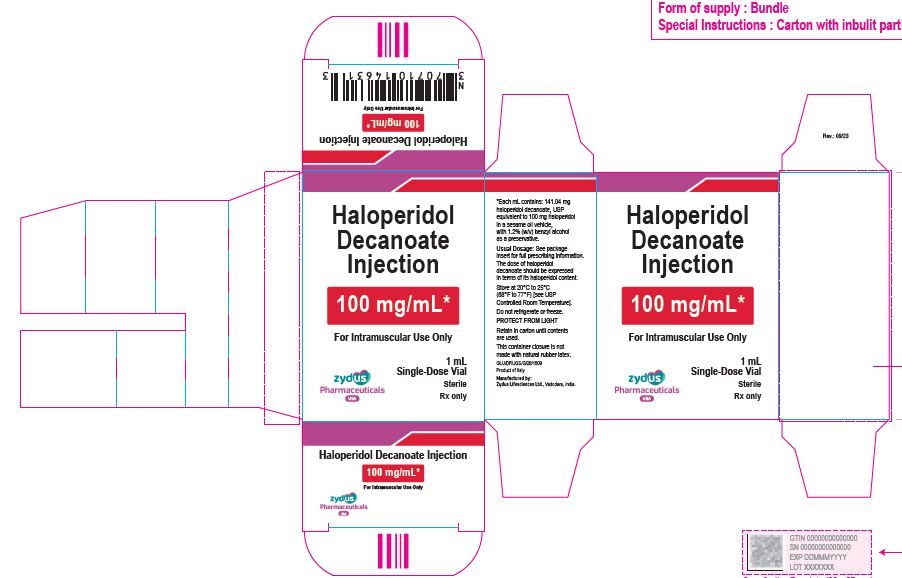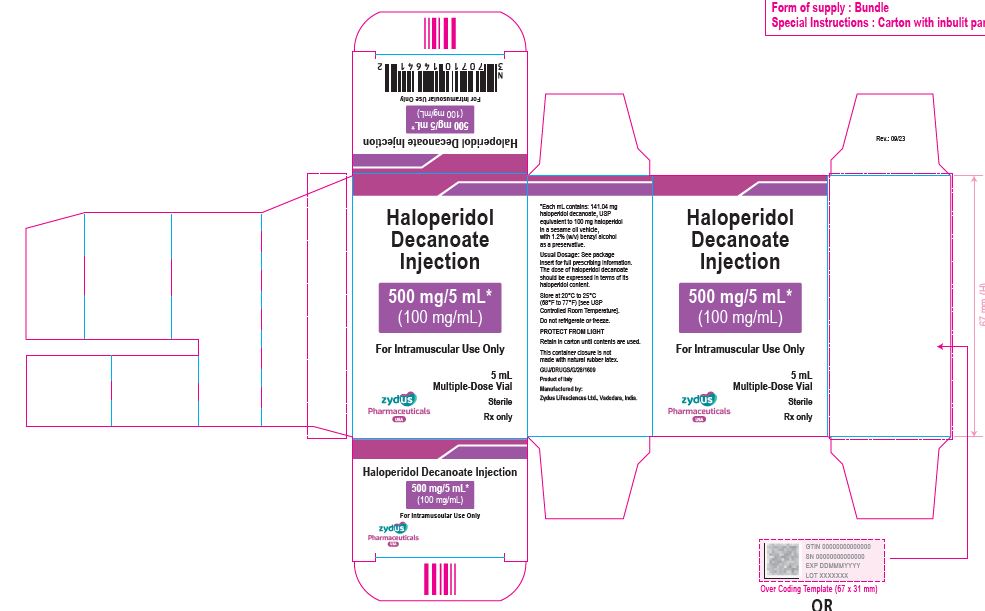 DRUG LABEL: Haloperidol decanoate
NDC: 70771-1851 | Form: INJECTION
Manufacturer: Zydus Lifesciences Limited
Category: prescription | Type: HUMAN PRESCRIPTION DRUG LABEL
Date: 20230901

ACTIVE INGREDIENTS: HALOPERIDOL DECANOATE 50 mg/1 mL
INACTIVE INGREDIENTS: SESAME OIL; BENZYL ALCOHOL

Haloperidol Decanoate Injection
For Intramuscular Injection Only

PACKAGE LABEL.PRINCIPAL DISPLAY PANEL

50 mg/mL Carton (3 vials per carton)

NDC 70771-1851-9

Haloperidol Decanoate

Injection

50 mg/mL*

For Intramuscular Use Only

3 X 1 mL

Single-Dose Vials

Sterile

Rx only

250 mg/5 mL (50 mg/mL) Carton (1 vial per carton)

NDC 70771-1852-1

Haloperidol Decanoate Injection

250 mg/5 mL*

(50 mg/mL)

For Intramuscular Use Only

5 mL

Multiple-Dose Vial

Sterile

Rx only

100 mg/mL Carton (1 vial per carton)

NDC 70771-1853-1

Haloperidol Decanoate Injection

100 mg/mL*

For Intramuscular Use Only

1 mL

Single-Dose Vial

Sterile

Rx only

500 mg/5 mL (100 mg/mL) Carton (1 vial per carton)

NDC 70771-1854-1

Haloperidol Decanoate Injection

500 mg/5 mL*

(100 mg/mL)

For Intramuscular Use Only

5 mL Multiple-Dose Vial

Sterile

Rx only